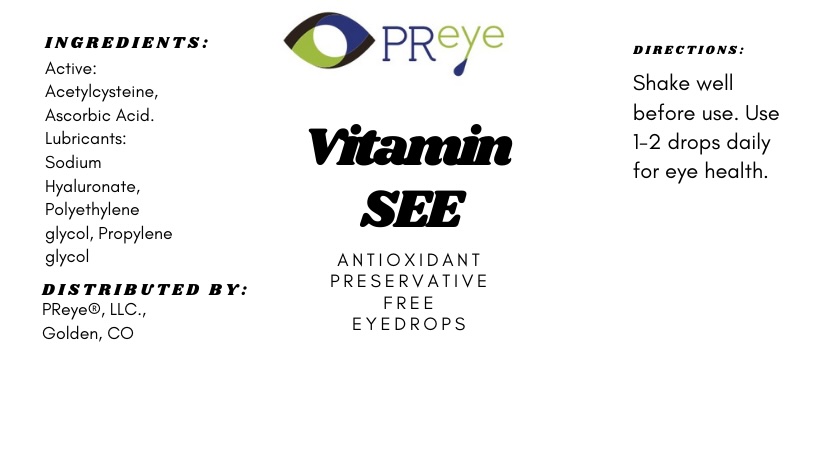 DRUG LABEL: VITAMIN SEE by PReye
NDC: 84420-4855 | Form: LIQUID
Manufacturer: PReye LLC
Category: otc | Type: HUMAN OTC DRUG LABEL
Date: 20240627

ACTIVE INGREDIENTS: ACETYLCYSTEINE 3.3 mg/1 mL; ASCORBIC ACID 8.3 mg/1 mL
INACTIVE INGREDIENTS: HYALURONIC ACID

VITAMIN SEE By PReye

Acetylcysteine, Ascorbic Acid

VITAMIN SEE By PReye

1-2 drops twice daily

VITAMIN SEE By PReye

Indications: For General Eye Health

VITAMIN SEE By PReye

No Need to keep out of reach of children

VITAMIN SEE By PReye

Indications: For General Eye Health

VITAMIN SEE By PReye

For General Eye Health

VITAMIN SEE By PReye

No warnings

INACTIVE INGREDIENT

Hyaluronic Acid

VITAMIN SEE By PReye

Vitamin SEE Label.jpg